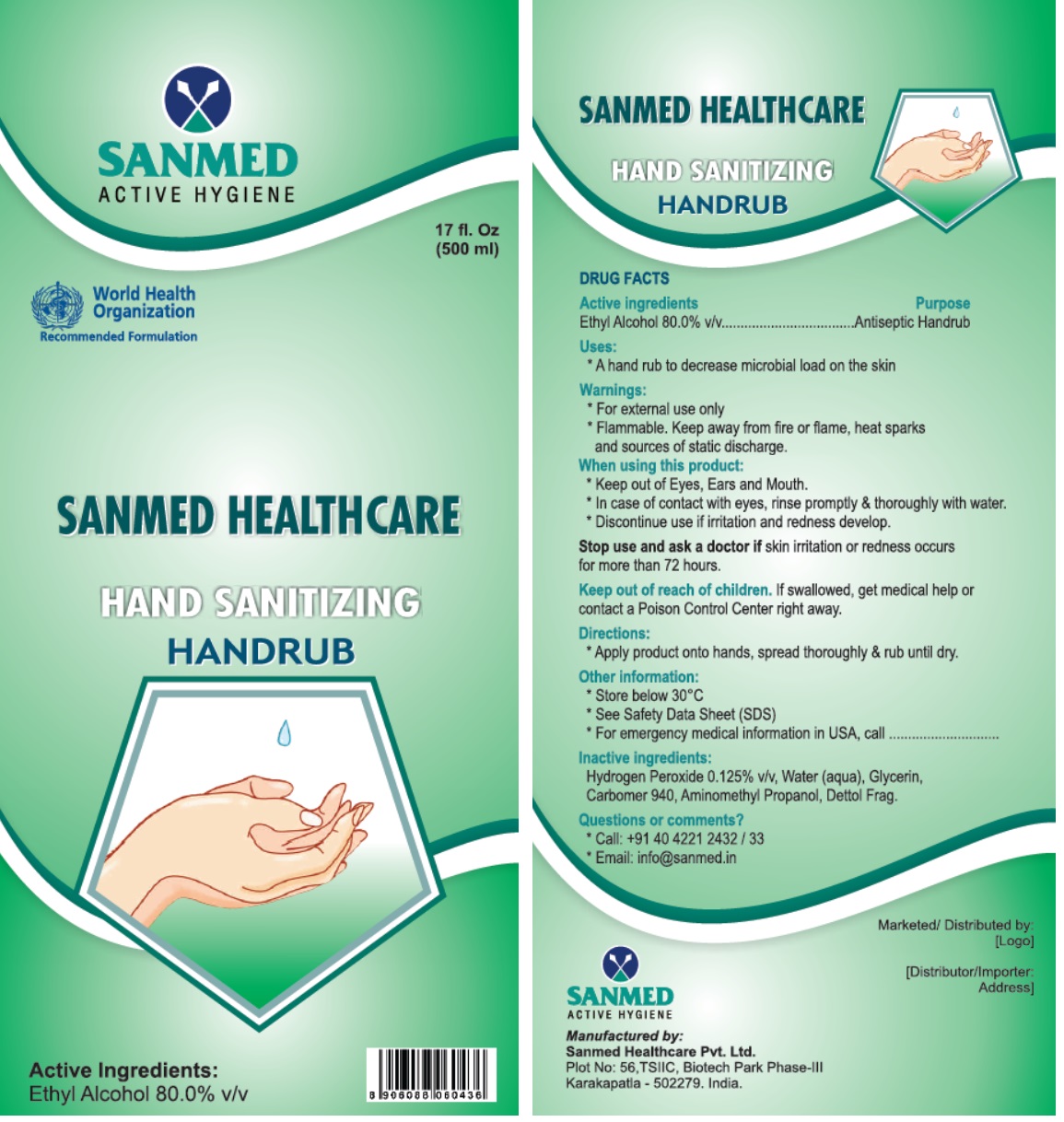 DRUG LABEL: SANMED HEALTHCARE HAND SANITIZING HANDRUB
NDC: 81357-103 | Form: LIQUID
Manufacturer: Sanmed Healthcare Private Limited
Category: otc | Type: HUMAN OTC DRUG LABEL
Date: 20210520

ACTIVE INGREDIENTS: ALCOHOL 80 mL/100 mL
INACTIVE INGREDIENTS: HYDROGEN PEROXIDE; WATER; GLYCERIN; CARBOMER HOMOPOLYMER TYPE C (ALLYL PENTAERYTHRITOL CROSSLINKED); AMINOMETHYLPROPANOL

SANMED HEALTHCARE HAND SANITIZING HANDRUB

Active ingredients

Ethyl Alcohol 80.0% v/v

Purpose

Antiseptic Handrub

Uses:

* A hand rub to decrease microbial load on the skin

Warnings:

* For external use only
* Flammable. Keep away from fire or flame, heat sparks and sources of static discharge

When using this product:
* Keep out of Eyes, Ears and Mouth.
* In case of contact with eyes, rinse promptly & thoroughly with water.
* Discontinue use if irritation and redness develop.

Stop use and ask a doctor if skin irritation or redness occurs for more than 72 hours.

Keep out of reach of children. If swallowed, get medical help or contact a Poison Control Center right away.

Directions:

* Apply product onto hands, spread thoroughly & rub until dry.

Other information:

* Store below 30°C
* See Safety Data Sheet (SDS)
* For emergency medical information in USA, call

Inactive ingredients:

Hydrogen Peroxide 0.125% v/v, Water (aqua), Glycerin, Carbomer 940, Aminomethyl Propanol, Dettol Frag.

Questions or comments?

* Call: +91 40 4221 2432 / 33
* Email: info@sanmed.in

World Health Organization Recommended Formulation

SANMED ACTIVE HYGIENE

Manufactured by:
Sanmed Healthcare Pvt. Ltd.
Plot No: 56, TSIIC, Biotech Park Phase-III
Karakapatla - 502279. India.